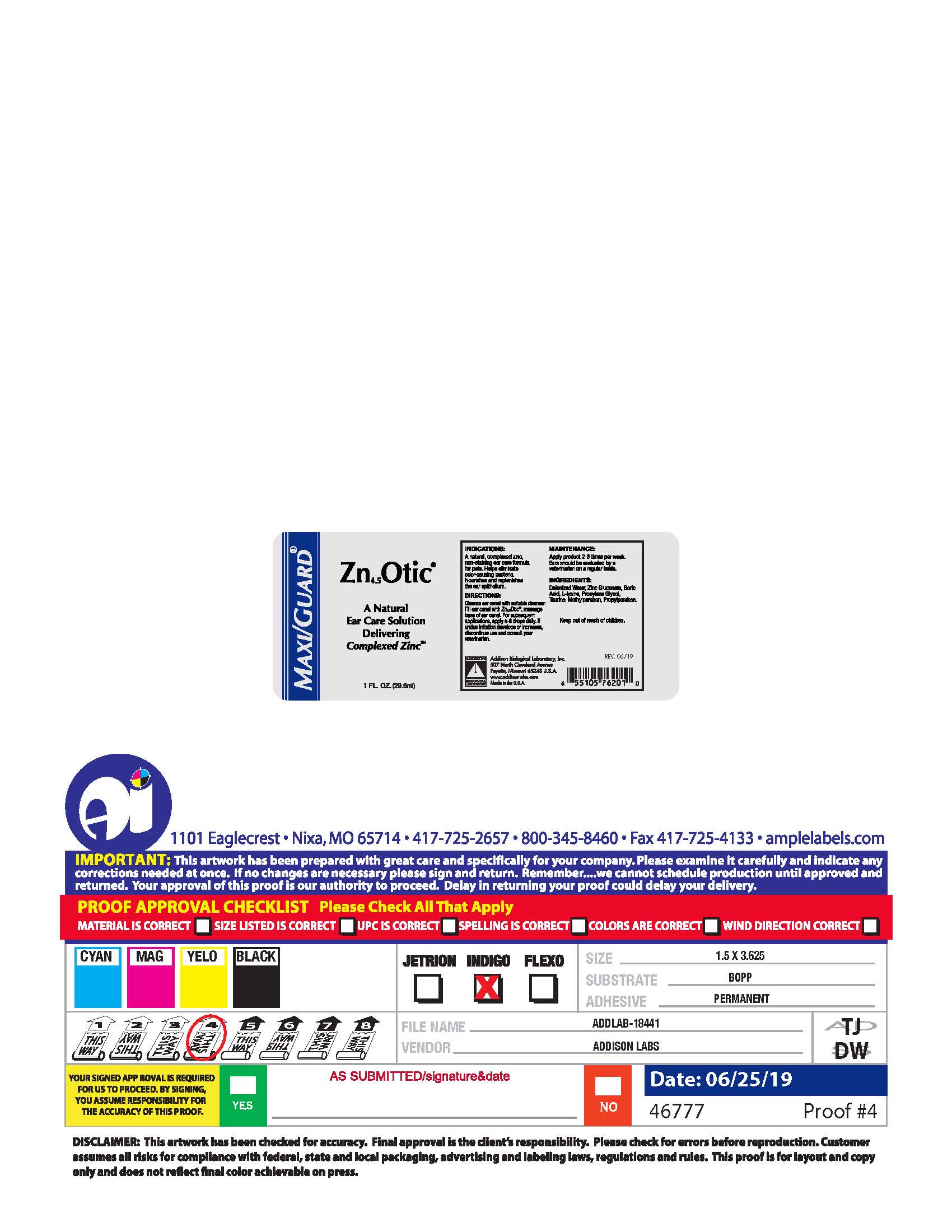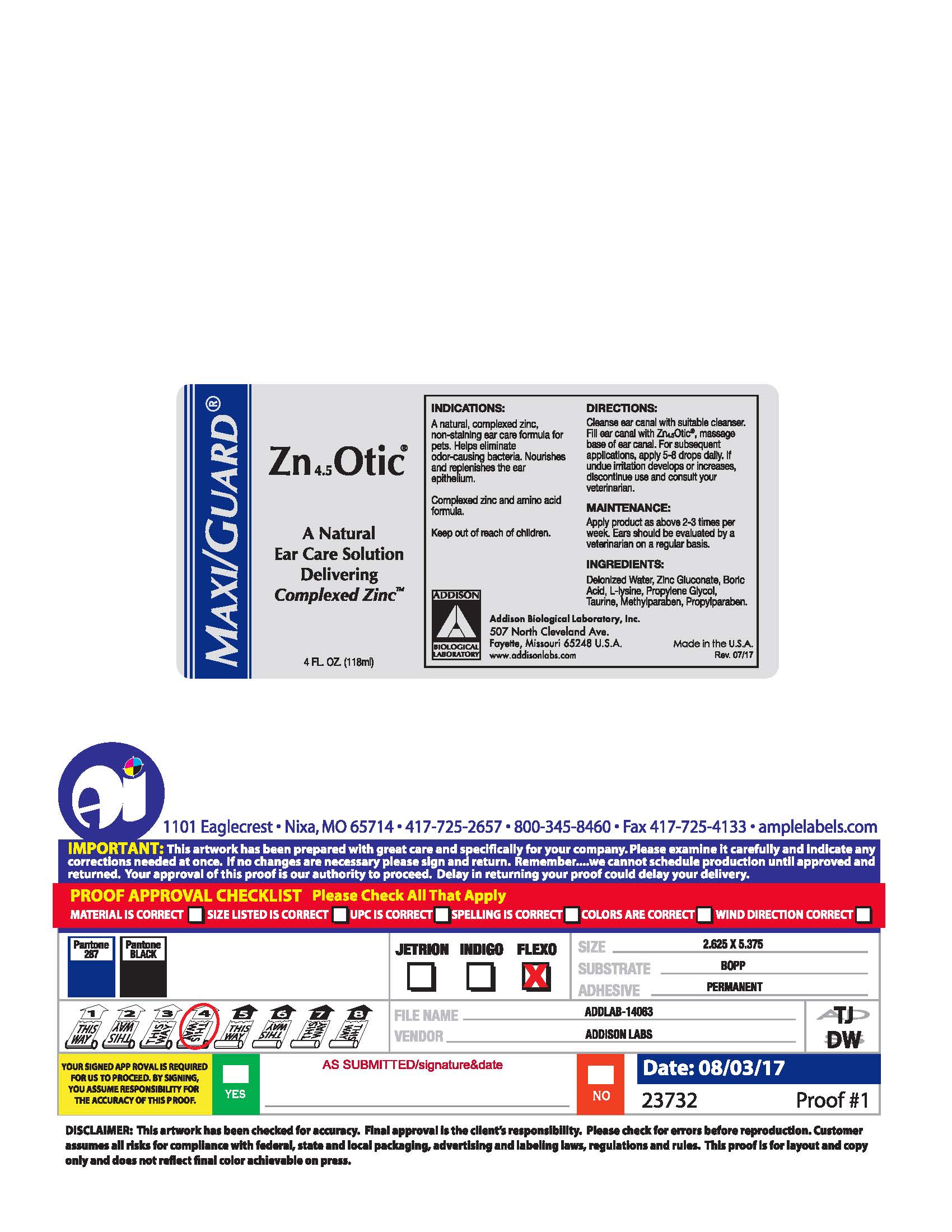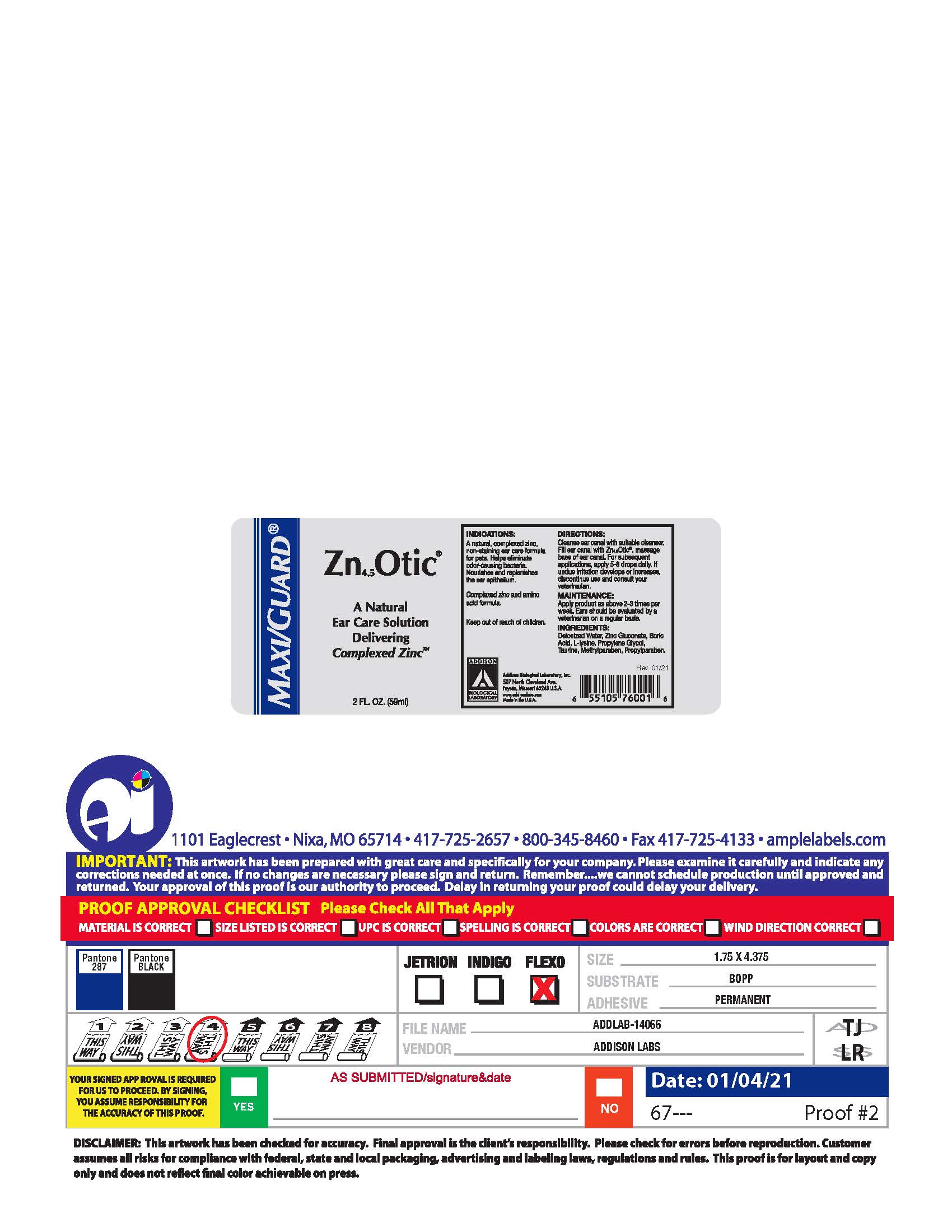 DRUG LABEL: Zn4.5Otic
NDC: 86045-5000 | Form: SOLUTION
Manufacturer: Addison Biological Laboratory, Inc.
Category: animal | Type: OTC ANIMAL DRUG LABEL
Date: 20251201

ACTIVE INGREDIENTS: ZINC GLUCONATE .011 g/1 mL
INACTIVE INGREDIENTS: WATER; TAURINE; METHYLPARABEN; PROPYLPARABEN; LYSINE; BORIC ACID; PROPYLENE GLYCOL

Zn4.5Otic®

INDICATIONS:

A natural, complexed zinc, non-staining ear care formula for pets. Helps eliminate odor-causing bacteria. Nourishes and replenishes the ear epithelium.

INFORMATION FOR OWNERS/CAREGIVERS

Complexed zinc and amino acid formula.

Keep out of reach of children.

DIRECTIONS:

Cleanse ear canal with suitable cleanser. Fill ear canal with Zn4.5Otic, massage base of ear canal. For subsequent applications, apply 5-8 drops daily. If undue irritation develops or increases, discontinue use and consult your veterinarian.

ROUTE, METHOD AND FREQUENCY OF ADMINISTRATION

MAINTENANCE:

Apply product as above 2-3 times per week. Ears should be evaluated by a veterinarian on a regular basis.

INGREDIENTS:

Deionized Water, Zinc Gluconate, BoriC Acid, L-Lysine, Propylene Glycol, Taurine, Methylparaben, Propylparaben.

Addison Biological Laboratory, Inc.
507 North Cleveland Avenue
Fayette, Missouri 65248 U.S.A.
www.addisonlabs.com
MADE IN THE U.S.A.
Rev. 05/13

PACKAGE LABEL

MAXI/GUARD®
Zn4.5Otic®
A Natural
Ear Care Solution
Delivering
Complexed Zinc™
1 FL. OZ. (29.5mL)
INDICATIONS:
A natural, complexed zinc,
non-staining ear care formula
for pets. Helps eliminateodor-causing bacteria.
Nourishes and replenishes
the ear epithelium.
Complexed zinc and amino
acid formula.
Keep out of reach of children.
DIRECTIONS:
Cleanse ear canal with suitable cleanser.
Fill ear canal with Zn4.5Otic®, massage
base of ear canal. For subsequent
applications, apply 5-8 drops daily. If
undue irritation develops or increases,
discontinue use and consult your
veterinarian.
MAINTENANCE:
Apply product as above 2-3 times per
week. Ears should be evaluated by a
veterinarian on a regular basis.
INGREDIENTS:
Deionized Water, Zinc Gluconate, Boric Acid,
L-Lysine, Propylene Glycol,
Taurine, Methylparaben, Propylparaben.

Addison Biological Laboratory, Inc.
507 North Cleveland Avenue
Fayette, Missouri 65248 U.S.A.
www.addisonlabs.com
MADE IN THE U.S.A.
Rev. 06/19

PACKAGE LABEL

MAXI/GUARD®
Zn4.5Otic®
A Natural
Ear Care Solution
Delivering
Complexed Zinc™
2 FL. OZ. (59mL)
INDICATIONS:
A natural, complexed zinc,
non-staining ear care formula
for pets. Helps eliminate
odor-causing bacteria.
Nourishes and replenishes
the ear epithelium.
Complexed zinc and amino
acid formula.
Keep out of reach of children.
DIRECTIONS:
Cleanse ear canal with suitable cleanser.
Fill ear canal with Zn4.5Otic®, massage
base of ear canal. For subsequent
applications, apply 5-8 drops daily. If
undue irritation develops or increases,
discontinue use and consult your
veterinarian.
MAINTENANCE:
Apply product as above 2-3 times per
week. Ears should be evaluated by a
veterinarian on a regular basis.
INGREDIENTS:
Deionized Water, Zinc Gluconate, Boric Acid,
L-Lysine, Propylene Glycol,
Taurine, Methylparaben, Propylparaben.
Addison Biological Laboratory, Inc.
507 North Cleveland Avenue
Fayette, Missouri 65248 U.S.A.
www.addisonlabs.com
MADE IN THE U.S.A.
Rev. 01/21

PACKAGE LABEL

MAXI/GUARD®
Zn4.5Otic®
A Natural
Ear Care Solution
Delivering
Complexed Zinc™
4 FL. OZ. 118mL)
INDICATIONS:
A natural, complexed zinc,
non-staining ear care formula
for pets. Helps eliminate
odor-causing bacteria.
Nourishes and replenishes
the ear epithelium.
Complexed zinc and amino
acid formula.
Keep out of reach of children.
DIRECTIONS:
Cleanse ear canal with suitable cleanser.
Fill ear canal with Zn4.5Otic®, massage
base of ear canal. For subsequent
applications, apply 5-8 drops daily. If
undue irritation develops or increases,
discontinue use and consult your
veterinarian.
MAINTENANCE:
Apply product as above 2-3 times per
week. Ears should be evaluated by a
veterinarian on a regular basis.
INGREDIENTS:
Deionized Water, Zinc Gluconate, Boric Acid,
L-Lysine, Propylene Glycol,
Taurine, Methylparaben, Propylparaben.
Addison Biological Laboratory, Inc.
507 North Cleveland Avenue
Fayette, Missouri 65248 U.S.A.
www.addisonlabs.com
MADE IN THE U.S.A.
Rev. 07/17